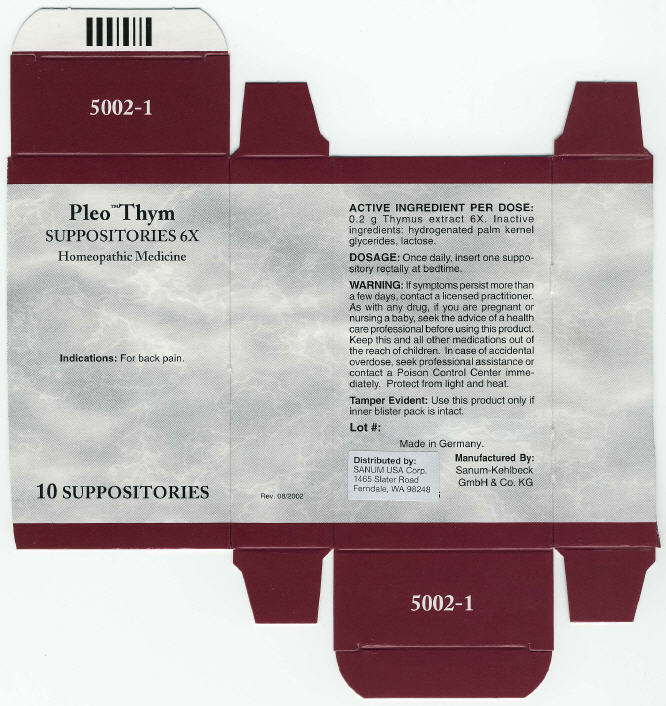 DRUG LABEL: PLEO THYM
NDC: 60681-5002 | Form: SUPPOSITORY
Manufacturer: Sanum Kehlbeck GmbH & Co. KG
Category: homeopathic | Type: HUMAN OTC DRUG LABEL
Date: 20110801

ACTIVE INGREDIENTS: BOS TAURUS THYMUS 6 [hp_X]/1 1
INACTIVE INGREDIENTS: lactose

Pleo™ Thym
SUPPOSITORIES 6X

PURPOSE

Homeopathic Medicine

10 SUPPOSITORIES

Indications

For back pain.

ACTIVE INGREDIENT PER DOSE

0.2 g Thymus extract 6X.

Inactive ingredients

hydrogenated palm kernel glycerides, lactose.

DOSAGE

Once daily, insert one suppository rectally at bedtime.

WARNING

If symptoms persist more than a few days, contact a licensed practitioner. As with any drug, if you are pregnant or nursing a baby, seek the advice of a health care professional before using this product.

KEEP OUT OF REACH OF CHILDREN

Keep this and all other medications out of the reach of children. In case of accidental overdose, seek professional assistance or contact a Poison Control Center immediately.

STORAGE AND HANDLING

Protect from light and heat.

Tamper Evident

Use this product only if inner blister pack is intact.

Made in Germany.

Distributed by:
SANUM USA Corp.
1465 Slater Road
Ferndale, WA 98248

Manufactured By:
Sanum-Kehlbeck
GmbH & Co. KG

Rev. 08/2002

PRINCIPAL DISPLAY PANEL - 10 Suppositories Carton

Pleo™ Thym
SUPPOSITORIES 6X

Homeopathic Medicine

Indications: For back pain.

10 SUPPOSITORIES